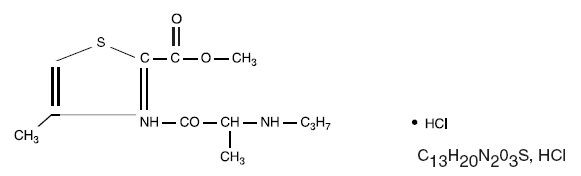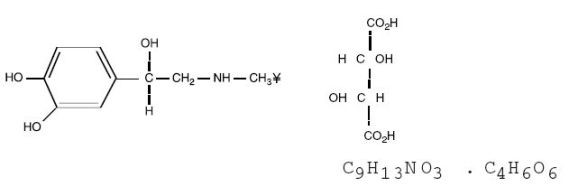 DRUG LABEL: Unknown
Manufacturer: SEPTODONT, Inc.
Category: prescription | Type: HUMAN PRESCRIPTION DRUG LABELING
Date: 20061226

Septocaine®
(articaine hydrochloride 4% (40 mg/mL)
with epinephrine 1:100,000 injection)

For Infiltration and Nerve Block Anesthesia

DESCRIPTION

Septocaine® injection is a sterile, aqueous solution that contains articaine HCl 4% (40mg/mL) with epinephrine bitartrate in a 1:100,000 strength. Articaine HCl is a local anesthetic, which is chemically designated as 4-methyl-3-[2-(propylamino)-propionamido]-2-thiophene-carboxylic acid, methyl ester hydrochloride and is a racemic mixture. Articaine HCl has a molecular weight of 320.84 and the molecular and structural formulae are displayed below :

Articaine HCl has a partition coefficient in n-octanol/ Soerensen buffer (pH : 7.35) of 17 and a pKa of 7.8.

Epinephrine bitartrate, (-)-1-(3,4-Dihydroxyphenyl)-2-methylamino-ethanol (+) tartrate (1:1) salt, is a vasoconstrictor that is added to articaine HCl in a concentration of 1:100,000 as the free base. It has a molecular weight of 333.3. The molecular and structural formulae are displayed below:

Septocaine® contains articaine HCl (40mg/mL), epinephrine as bitartrate (1:100,000), sodium chloride (1.6 mg/mL), and sodium metabisulfite (0.5 mg/mL). The product is formulated with a 15% overage of epinephrine. The pH is adjusted to 5.0 with sodium hydroxide.

CLINICAL PHARMACOLOGY

Pharmacokinetics

Absorption

Following dental injection by the submucosal route of an articaine solution containing 1:200,000 epinephrine, articaine reaches peak blood concentration about 25 minutes after a single dose injection and 48 minutes after three doses. Peak plasma levels of articaine achieved after 68 and 204 mg doses are 385 and 900 ng/mL, respectively.

Distribution

Approximately 60 to 80% of articaine HCl is bound to human serum albumin and γ-globulins at 37°C in vitro.

Metabolism

Articaine HCl is rapidly metabolized by plasma carboxyesterase to its primary metabolite, articainic acid, which is inactive. In vitro studies show that the human liver microsome P450 isoenzyme system metabolizes approximately 5% to 10% of available articaine with nearly quantitative conversion to articainic acid.

Excretion

The elimination half-life of articaine is about 1.8 hours and that of articainic acid is about 1.5 hours. Articaine is excreted primarily through urine with 53 - 57% of the administered dose eliminated in the first 24 hours following submucosal administration. Articainic acid is the primary metabolite in urine. A minor metabolite, articainic acid glucuronide, is also excreted in urine. Articaine constitutes only 2% of the total dose excreted in urine.

Special populations

Effect of Age

No studies have been performed to evaluate the pharmacokinetics of Septocaine® injection in geriatric or pediatric subjects.

Race

There is insufficient information to determine whether the pharmacokinetics of Septocaine® injection differs by race.

Renal and Hepatic Insufficiency

No studies have been performed with Septocaine® injection in patients with renal or hepatic dysfunction.

Pharmacodynamics

Mechanism of action

Articaine HCl is a member of the amino amide class of local anesthetics. Local anesthetics block the generation and conduction of nerve impulses, presumably by increasing the threshold for electrical excitation in the nerve, by slowing the propagation of the nerve impulse, and by reducing the rate of rise of the action potential. In general, the progression of anesthesia is related to the diameter, myelination and conduction velocity of the affected nerve fibers. Clinically, the order of loss of nerve function is as follows: (1) pain, (2) temperature, (3) touch, (4) proprioception, and (5) skeletal muscle tone. Epinephrine is a vasoconstrictor added to articaine HCl to slow absorption into the general circulation and thus prolong maintenance of an active tissue concentration.

The onset of anesthesia following administration of Septocaine® has been shown to be within 1 to 6 minutes of injection. Complete anesthesia lasts approximately 1 hour.

Administration of articaine HCl with epinephrine results in a 3- to 5-fold increase in plasma epinephrine concentrations compared to baseline; however, in heathly adults it does not appear to be associated with marked increases in blood pressure or heart rate, except in the case of accidental intravascular injection (See WARNINGS).

CLINICAL TRIALS

Three randomized, double-blind, active-controlled studies were designed to evaluate effectiveness of Septocaine® as a dental anesthetic. A total of 882 patients received Septocaine®. Of these, 7% were between 4 and 16 years old, 87% were between 17 and 65 years old, and 6% were at least 65 years old. In addition, 53% of patients were female and 47% were male, with a racial/ethnic distribution of 73% white, 11% Hispanic, 8% black, 5% Asian, and 3%"other" races/ ethnicities. These patients underwent simple dental procedures such as single uncomplicated extractions, routine operative procedures, single apical resections, and single crown procedures, and complex dental procedures such as multiple extractions, multiple crowns and/or bridge procedures, multiple apical resections, alveolectomies, muco-gingival operations, and other surgical procedures on the bone. Septocaine™ was administered as submucosal infiltration and/or nerve block. Efficacy was measured immediately following the procedure by having the patient and investigator rate the patient's procedural pain using a 10 cm visual analog scale (VAS), in which a score of zero represented no pain, and a score of 10 represented the worst pain imaginable.

Mean patient and investigator VAS pain scores were 0.3 - 0.4 cm for simple procedures and 0.5 - 0.6 cm for complex procedures. These values are summarized in Table 1.

Table 1. Summary of VAS Pain Scores
 | Septocaine® (articaine HCl 4% with epinephrine 1:100,000)
 | Simple procedures | Complex procedures
Number of patients | 674 | 207
Investigator score (cm)
Mean | 0.3 | 0.5
Median | 0.0 | 0.2
Range | 0 - 9.0 | 0 - 7.3
Patient score (cm)
Mean | 0.4 | 0.6
Median | 0.0 | 0.2
Range | 0 - 8.0 | 0 - 8.7

INDICATIONS AND USAGE

Septocaine® is indicated for local, infiltrative, or conductive anesthesia in both simple and complex dental and periodontal procedures.

CONTRAINDICATIONS

Septocaine® is contraindicated in patients with a known history of hypersensitivity to local anesthetics of the amide type, or in patients with known hypersensitivity to sodium metabisulfite.

WARNINGS

ACCIDENTAL INTRAVASCULAR INJECTION MAY BE ASSOCIATED WITH CONVULSIONS, FOLLOWED BY CENTRAL NERVOUS SYSTEM OR CARDIORESPIRATORY DEPRESSION AND COMA, PROGRESSING ULTIMATELY TO RESPIRATORY ARREST. DENTAL PRACTITIONERS AND/OR CLINICIANS WHO EMPLOY LOCAL ANESTHETIC AGENTS SHOULD BE WELL VERSED IN DIAGNOSIS AND MANAGEMENT OF EMERGENCIES THAT MAY ARISE FROM THEIR USE. RESUSCITATIVE EQUIPMENT, OXYGEN, AND OTHER RESUSCITATIVE DRUGS SHOULD BE AVAILABLE FOR IMMEDIATE USE.

Intravascular injections should be avoided. To avoid intravascular injection, aspiration should be performed before Septocaine® is injected. The needle must be repositioned until no return of blood can be elicited by aspiration. Note, however, that the absence of blood in the syringe does not guarantee that intravascular injection has been avoided.

Septocaine® contains epinephrine that can cause local tissue necrosis or systemic toxicity. Usual precautions for epinephrine administration should be observed.

Septocaine® contains sodium metabisulfite, a sulfite that may cause allergic-type reactions including anaphylactic symptoms and life-threatening or less severe asthmatic episodes in certain susceptible people. The overall prevalence of sulfite sensitivity in the general population is unknown. Sulfite sensitivity is seen more frequently in asthmatic than in non-asthmatic people.

PRECAUTIONS

General

Resuscitative equipment, oxygen, and other resuscitative drugs should be available for immediate use (See WARNINGS). The lowest dosage that results in effective anesthesia should be used to avoid high plasma levels and serious adverse effects. Repeated doses of Septocaine® may cause significant increases in blood levels with each repeated dose because of possible accumulation of the drug or its metabolites. Tolerance to elevated blood levels varies with the status of the patient. Debilitated patients, elderly patients, acutely ill patients and pediatric patients should be given reduced doses commensurate with their age and physical condition. Septocaine® should also be used with caution in patients with heart block.

Local anesthetic solutions, such as Septocaine®, containing a vasoconstrictor should be used cautiously. Patients with peripheral vascular disease and those with hypertensive vascular disease may exhibit exaggerated vasoconstrictor response. Ischemic injury or necrosis may result. Septocaine® should be used with caution in patients during or following the administration of potent general anesthetic agents, since cardiac arrhythmias may occur under such conditions.

Systemic absorption of local anesthetics can produce effects on the central nervous and cardiovascular systems. At blood concentrations achieved with therapeutic doses, changes in cardiac conduction, excitability, refractoriness, contractility, and peripheral vascular resistance are minimal. However, toxic blood concentrations depress cardiac conduction and excitability, which may lead to atrioventricular block, ventricular arrhythmias, and cardiac arrest, sometimes resulting in fatalities. In addition, myocardial contractility is depressed and peripheral vasodilation occurs, leading to decreased cardiac output and arterial blood pressure.

Careful and constant monitoring of cardiovascular and respiratory (adequacy of ventilation) vital signs and the patient's state of consciousness should be accomplished after each local anesthetic injection. It should be kept in mind at such times that restlessness, anxiety, tinnitus, dizziness, blurred vision, tremors, depression, or drowsiness may be early warning signs of central nervous system toxicity.

In vitro studies show that about 5% to 10% of articaine is metabolized by the human liver microsomal P450 isoenzyme system. However, because no studies have been performed in patients with liver dysfunction, caution should be used in patients with severe hepatic disease. Septocaine® should also be used with caution in patients with impaired cardiovascular function since they may be less able to compensate for functional changes associated with the prolongation of A-V conduction produced by these drugs.

Small doses of local anesthetics injected in dental blocks may produce adverse reactions similar to systemic toxicity seen with unintentional intravascular injections of larger doses. Confusion, convulsions, respiratory depression and/or respiratory arrest, and cardiovascular stimulation or depression have been reported. These reactions may be due to intra-arterial injection of the local anesthetic with retrograde flow to the cerebral circulation. Patients receiving these blocks should be observed constantly. Resuscitative equipment and personnel for treating adverse reactions should be immediately available.

Dosage recommendations should not be exceeded.

(See DOSAGE and ADMINISTRATION.)

Information for Patients

The patient should be informed in advance of the possibility of temporary loss of sensation and muscle function following infiltration and nerve block injections.

Clinically Significant Drug Interactions

The administration of local anesthetic solutions containing epinephrine to patients receiving monoamine oxidase inhibitors or tricyclic antidepressants may produce severe, prolonged hypertension. Phenothiazines and butyrophenones may reduce or reverse the pressor effect of epinephrine. Concurrent use of these agents should generally be avoided. In situations when concurrent therapy is necessary, careful patient monitoring is essential.

Carcinogenesis, Mutagenesis, Impairment of Fertility :

Studies to evaluate the carcinogenic potential of Articaine HCl in animals have not been conducted. Five standard mutagenicity tests, including three in vitro tests (the nonmammalian Ames test, the mammalian Chinese hamster ovary chromosomal aberration test and a mammalian gene mutation test with articaine HCl) and two in vivo mouse micronucleous tests (one with Septocaine® and one with articaine HCl alone) showed no mutagenic effects. No effects on male or female fertility were observed in rats for Septocaine® administered subcutaneously in doses up to 80 mg/kg/day (approximately two times the maximum male and female recommended human dose on a mg/m^2 basis).

Pregnancy

Teratogenic Effects-Pregnancy Category C

In developmental studies, no embryofetal toxicities were observed when Septocaine® was administered subcutaneously throughout organogenesis at doses up to 40 mg/kg in rabbits and 80 mg/kg in rats (approximately 2 times the maximun recommended human dose on a mg/m^2 basis). In rabbits, 80 mg/kg (approximately 4 times the maximun recommended human dose on a mg/m^2 basis) did cause fetal death and increase fetal skeletal variations, but these effects may be attributable to the severe maternal toxicity, including seizures, observed at this dose.

When articaine hydrochloride was administered subcutaneously to rats throughout gestation and lactation, 80 mg/kg (approximately 2 times the maximun recommended human dose on a mg/m^2 basis) increased the number of stilbirths and adversely affected passive avoidance, a measure of learning, in pups. This dose also produced severe maternal toxicity in some animals. A dose of 40 mg/kg (approximately equal to the maximun recommended human dose on a mg/m^2 basis) did not produce these effects. A similar study using Septocaine® (articaine hydrochloride and epinephrine 1:100,000) rather than articaine hydrochloride alone produced maternal toxicity, but no effects on offspring.

There are no adequate and well-controlled studies in pregnant women. Animal reproduction studies are not always predictive of human response. Septocaine® should be used during pregnancy only if the potential benefit justifies the potential risk to the fetus.

Nursing Mothers

It is not known whether articaine is excreted in human milk. Because many drugs are excreted in human milk, caution should be exercised when Septocaine® is administered to a nursing woman.

Pediatric Use

In clinical trials, 61 pediatric patients between the ages of 4 and 16 years received Septocaine®. Among these pediatric patients, doses from 0.76 mg/kg to 5.65 mg/kg (0.9 to 5.1 mL) were administered safely to 51 patients for simple procedures and doses between 0.37 mg/kg and 7.48 mg/kg (0.7 to 3.9 mL) were administered safely to 10 patients for complex procedures. However, there was insufficient exposure to Septocaine® at doses greater than 7.00 mg/kg in order to assess its safety in pediatric patients. No unusual adverse events were noted in these patients. Approximately 13% of these pediatric patients required additional injections of anesthetic for complete anesthesia. Safety and effectiveness in pediatric patients below the age of 4 years have not been established. Dosages in pediatric patients should be reduced, commensurate with age, body weight, and physical condition. See DOSAGE AND ADMINISTRATION.

Geriatric Use

In clinical trials, 54 patients between the ages of 65 and 75 years, and 11 patients 75 years and over received Septocaine™. Among all patients between 65 and 75 years, doses from 0.43 mg/kg to 4.76 mg/kg (0.9 to 11.9 mL) were administered safely to 35 patients for simple procedures and doses from 1.05 mg/kg to 4.27 mg/kg (1.3 to 6.8 mL) were administered safely to 19 patients for complex procedures. Among the 11 patients ≥ 75 years old, doses from 0.78 mg/kg to 4.76 mg/kg (1.3 to 11.9 mL) were administered safely to 7 patients for simple procedures and doses of 1.12 mg/kg to 2.17 mg/kg (1.3 to 5.1 mL) were administered to 4 patients for complex procedures.

No overall differences in safety or effectiveness were observed between elderly subjects and younger subjects, and other reported clinical experience has not identified differences in responses between the elderly and younger patients, but greater sensitivity of some older individuals cannot be ruled out. Approximately 6% of patients between the ages of 65 and 75 years and none of the 11 patients 75 years of age or older required additional injections of anesthetic for complete anesthesia compared with 11% of patients between 17 and 65 years old who required additional injections.

ADVERSE REACTIONS

Reactions to Septocaine® are characteristic of those associated with other amide-type local anesthetics. Adverse reactions to this group of drugs may also result from excessive plasma levels, which may be due to overdosage, unintentional intravascular injection, or slow metabolic degradation.

The reported adverse events are derived from clinical trials in the US and UK. Of the 1325 patients treated in the primary clinical trials, 882 were exposed to Septocaine®.

Table 2. Adverse Events in controlled trials with an incidence of 1% or greater in patients administered Septocaine® (articaine hydrochloride 4% (40 mg/mL) with epinephrine 1:100,000 Injection).
Body system | Septocaine® N (%)
Number of Patients | 882 (100%)
Body As A Whole
Face Edema | 13 (1%)
Headache | 31 (4%)
Infection | 10 (1%)
Pain | 114 (13%)
Digestive System
Gingivitis | 13 (1%)
Nervous system
Paresthesia | 11 (1%)

The following list includes adverse and intercurrent events that were recorded in 1 or more patients, but occurred at an overall rate of less than one percent, and were considered clinically relevant.

Body as a Whole - abdominal pain, accidental injury, asthenia, back pain, injection site pain, malaise, neck pain.

Cardiovascular System - hemorrhage, migraine, syncope, tachycardia.

Digestive System - constipation, diarrhea, dyspepsia, glossitis, gum hemorrhage, mouth ulceration, nausea, stomatitis, tongue edemas, tooth disorder, vomiting.

Hemic and Lymphatic System - ecchymosis, lymphadenopathy.

Metabolic and Nutritional System - edema, thirst.

Musculoskeletal System - arthralgia, myalgia, osteomyelitis.

Nervous System - dizziness, dry mouth, facial paralysis, hyperesthesia, increased salivation, nervousness, neuropathy, paresthesia, somnolence.

Respiratory System - pharyngitis, rhinitis.

Skin and Appendages - pruritis, skin disorder.

Special Senses - ear pain, taste perversion.

Urogenital System - dysmenorrhea.

OVERDOSAGE

Acute emergencies from local anesthetics are generally related to high plasma levels encountered during therapeutic use of local anesthetics or to unintended subarachnoid injection of local anesthetic solution (see WARNINGS, PRECAUTIONS General and ADVERSE REACTIONS).

Management of Local Anesthetic Emergencies

The first consideration is prevention, best accomplished by careful and constant monitoring of cardiovascular and respiratory vital signs and the patient's state of consciousness after each local anesthetic injection. At the first sign of change, oxygen should be administered.

The first step in the management of convulsions, as well as hypoventilation, consists of immediate attention to the maintenance of a patent airway and assisted or controlled ventilation as needed. The adequacy of the circulation should be assessed. Should convulsions persist despite adequate respiratory support, treatment with appropriate anticonvulsant therapy is indicated. The practitioner should be familiar, prior to the use of local anesthetics, with the use of anticonvulsant drugs. Supportive treatment of circulatory depression may require administration of intravenous fluids and, when appropriate, a vasopressor.

If not treated immediately, both convulsions and cardiovascular depression can result in hypoxia, acidosis, bradycardia, arrhythmias and cardiac arrest. If cardiac arrest should occur, standard cardiopulmonary resuscitative measures should be instituted.

DOSAGE AND ADMINISTRATION

Table 3 (Recommended Dosages) summarizes the recommended volumes and concentrations of Septocaine® for various types of anesthetic procedures. The dosages suggested in this table are for normal healthy adults, administered by submucosal infiltration and/or nerve block.

Table 3. Recommended Dosages
PROCEDURE | Septocaine® Injection
 | Vol (mL) | Total Dose of Articaine (HCl) (mg)
Infiltration | 0.5-2.5 | 20-100
Nerve block | 0.5-3.4 | 20-136
Oral surgery | 1.0-5.1 | 40-204
THE ABOVE SUGGESTED VOLUMES SERVE ONLY AS A GUIDE. OTHER VOLUMES MAY BE USED PROVIDED THE TOTAL MAXIMUN RECOMMENDED DOSE IS NOT EXCEEDED.

These recommended doses serve only as a guide to the amount of anesthetic required for most routine procedures. The actual volumes to be used depend on a number of factors such as type and extent of surgical procedure, depth of anesthesia, degree of muscular relaxation, and condition of the patient. In all cases, the smallest dose that will produce the desired result should be given. Dosages should be reduced for pediatric patients, elderly patients, and patients with cardiac and/or liver disease. (See PRECAUTIONS, Pediatric Use and Geriatric Use).

The onset of anesthesia, and the duration of anesthesia are proportional to the volume and concentration (i.e., total dose) of local anesthetic used. Caution should be exercised when employing large volumes since the incidence of side effects may be dose-related.

MAXIMUM RECOMMENDED DOSAGES

Adults

For normal healthy adults, the maximum dose of articaine HCl administered by submucosal infiltration and/or nerve block should not exceed 7 mg/kg (0.175 mL/kg) or 3.2 mg/lb (0.0795 mL/lb) of body weight.

Pediatric Patients

Use in pediatric patients under 4 years of age is not recommended. The quantity to be injected should be determined by the age and weight of the child and the magnitude of the operation. Do not exceed the equivalent of 7 mg/kg (0.175 mL/kg) or 3.2 mg/lb (0.0795 mL/lb) of body weight.

STERILIZATION, STORAGE, AND TECHNICAL PROCEDURES

For chemical disinfection of the carpule, either isopropyl alcohol (91%) or ethyl alcohol (70%) is recommended. Many commercially available brands of isopropyl (rubbing) alcohol, as well as solutions of ethyl alcohol not of U.S.P. grade, contain denaturants that are injurious to rubber and therefore are not to be used.

Parenteral drug products should be inspected visually for particulate matter and discoloration prior to administration, whenever solution and container permit.

HOW SUPPLIED

Septocaine® (articaine HCl 4% with epinephrine 1:100,000 Injection) is available in 1.7 mL glass cartridges, in boxes or cans of 50 cartridges. The product is formulated with a 15% overage of epinephrine.

NDC 12862-1050-1 Can of 50 cartridges
NDC 12862-1050-2 Box of 50 cartridges

Store at 25°C (77°F) with brief excursions permitted between 15° and 30°C (59°F-86°F) (see USP controlled room temperature). Protect from light.

Manufactured in France by : SEPTODONT, France.

Distributed by : SEPTODONT, Inc.,
245, Quigley Boulevard-Suite C
New Castle, Delaware 19720

® 05 14 228 50 03
02/02